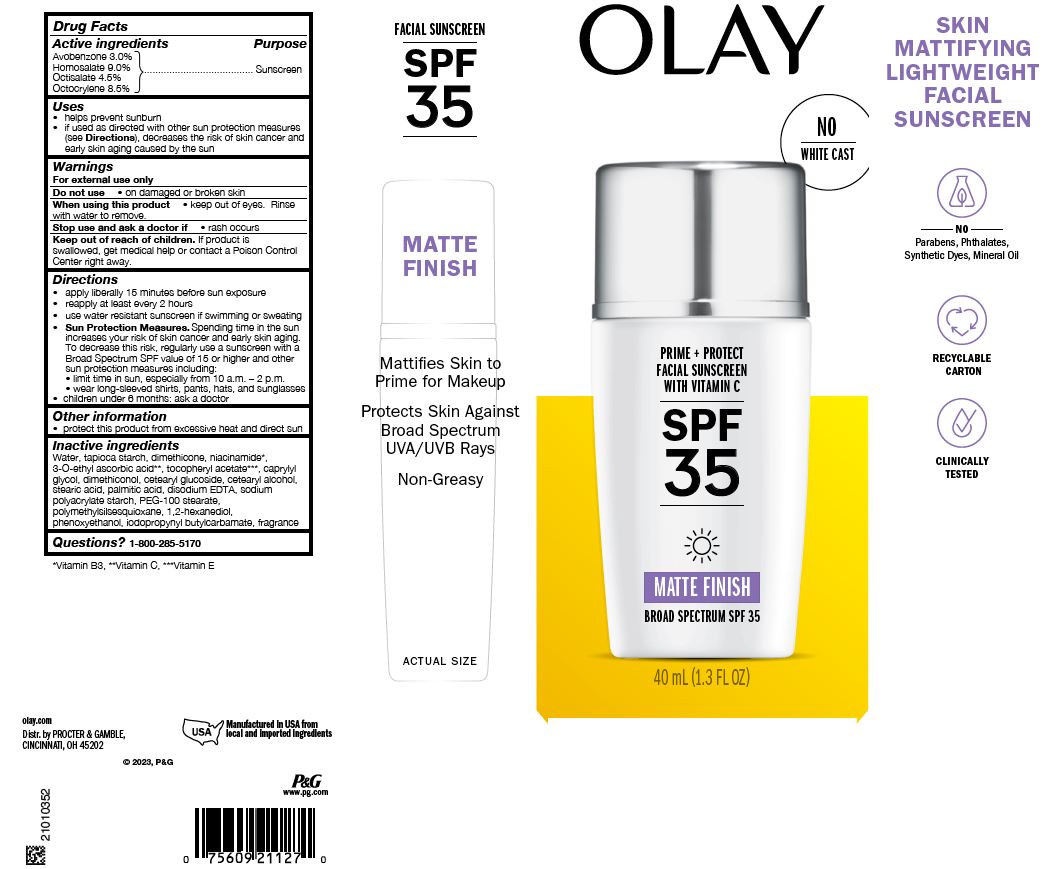 DRUG LABEL: Olay Glow plus Protect Sunscreen Dewy Glow SPF 50
NDC: 69423-741 | Form: STICK
Manufacturer: The Procter & Gamble Manufacturing Company
Category: otc | Type: HUMAN OTC DRUG LABEL
Date: 20251218

ACTIVE INGREDIENTS: AVOBENZONE 3 g/100 g; HOMOSALATE 10 g/100 g; OCTISALATE 5 g/100 g; OCTOCRYLENE 10 g/100 g
INACTIVE INGREDIENTS: POLYAMIDE-3 (12000 MW); CAPRYLYL GLYCOL; .ALPHA.-TOCOPHEROL ACETATE; POLYAMIDE-8 (4500 MW); ISOPROPYL ISOSTEARATE; BUTYLOCTYL SALICYLATE; HYLOCEREUS UNDATUS FRUIT; VINYLPYRROLIDONE/EICOSENE COPOLYMER; COCO-CAPRYLATE/CAPRATE; TETRAHEXYLDECYL ASCORBATE; SOYBEAN OIL; POLYGLYCERYL-3 DIISOSTEARATE; MEDIUM-CHAIN TRIGLYCERIDES; DIETHYLHEXYL SYRINGYLIDENEMALONATE; ALKYL (C12-15) BENZOATE; RUBUS CHAMAEMORUS SEED OIL; TOCOPHEROL; RICE GERM

Olay Glow + Protect Sunscreen Stick with Vitamin C SPF 50 Dewy Glow

Drug Facts

ACTIVE INGREDIENT

Avobenzone 3.0%

Homosalate 10.0%

Octisalate 5.0%

Octocrylene 10.0%

PURPOSE

Sunscreen

Uses

- helps prevent sunburn
- if used as directed with other sun protection measures (see Directions), decreases the risk of skin cancer and early skin aging caused by the sun

Warnings

For external use only

Do not use on damaged or broken skin

When using this product keep out of eyes. Rinse with water to remove.

Stop use and ask a doctor if rash occurs

Keep out of reach of children. If product is swallowed, get medical help or contact a Poison Control Center right away.

Directions

- apply liberally 15 minutes before sun exposure
- reapply at least every 2 hours
- use water resistant sunscreen if swimming or sweating
- Sun Protection Measures. Spending time in the sun increases your risk of skin cancer and early skin aging. To decrease this risk, regularly use a sunscreen with a Broad Spectrum SPF value of 15 or higher and other sun protection measures including:
  - limit time in sun, especially from 10 a.m. – 2 p.m.
  - wear long-sleeved shirts, pants, hats, and sunglasses
- children under 6 months: ask a doctor

Other information

- protect this product from excessive heat and direct sun

Inactive ingredients

Polyamide-8, C12-15 alkyl benzoate, coco-caprylate/caprate, isopropyl isostearate, butyloctyl salicylate, polyamide-3, VP/eicosene copolymer, tetrahexyldecyl ascorbate*, tocopheryl acetate**, tocopherol**, hylocereus undatus fruit extract, rubus chamaemorus seed oil, glycine soja (soybean) oil, caprylyl glycol, diethylhexyl syringylidenemalonate, polyglyceryl-3 diisostearate, oryza sativa (rice) germ extract, oryza sativa (rice) extract, caprylic/capric triglyceride

Questions or comments?

Call 1-800-285-5170

Dist. by PROCTER & GAMBLE,
CINCINNATI, OH 45202

PACKAGE LABEL

OLAY

GLOW + PROTECT

SUNSCREEN STICK WITH VITAMIN C

SPF 50

DEWY GLOW

BROAD SPECTRUM SPF 50

0.5 OZ (14 g)